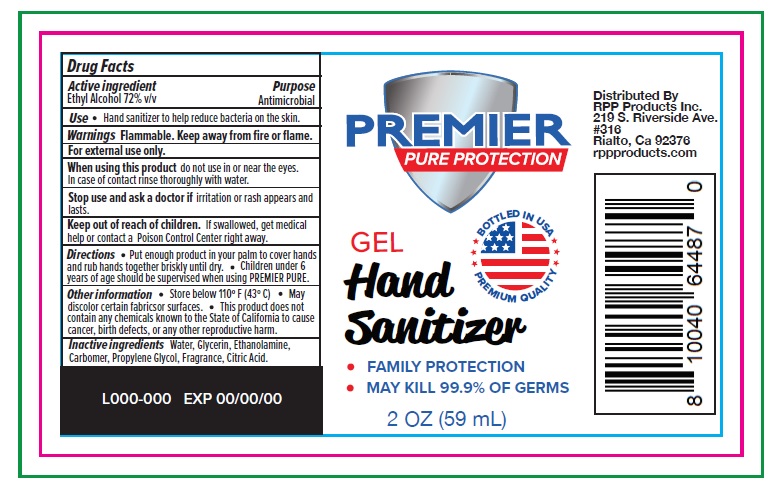 DRUG LABEL: PREMIER PURE Protection
NDC: 73945-004 | Form: GEL
Manufacturer: RPP PRODUCTS, INC.
Category: otc | Type: HUMAN OTC DRUG LABEL
Date: 20200505

ACTIVE INGREDIENTS: ALCOHOL 72 mL/100 mL
INACTIVE INGREDIENTS: WATER; GLYCERIN; MONOETHANOLAMINE; CARBOMER HOMOPOLYMER TYPE C (ALLYL PENTAERYTHRITOL CROSSLINKED); PROPYLENE GLYCOL; CITRIC ACID MONOHYDRATE

Active ingredient

Ethyl Alcohol 72% v/v

Purpose

Antimicrobial

Uses

hand sanitizer to help reduce bacteria on the skin

Warnings

Flammable, keep away from fire or flame

For external use only

When using this product do not use in or near the eyes

In case of contact rinse thoroughly with water

When using this product

do not use in or near the eyes. In case of contact, rinse eyes thoroughly with water

Stop use and ask doctor if

irritation or rash appears and lasts

Keep out of reach of children.

If swallowed, get medical help right away or contact a Poison Control Center immediately.

Directions

- Put enough product in your palm to cover hands and rub hands together briskly until dry.
- children under 6 years of age should be supervised when using this PREMIER PURE

Other information

- Store below 110^0 F (43^0C)
- May discolor certain fabrics or surfaces
- This product does not contain any chemicals known to the State of California to cause cancer, birth defects, or any other reproductive harm

Inactive ingredients

Water, Glycerin, Ethanolamine, Carbomer, Propylene Glycol, Fragrance, Citric Acid